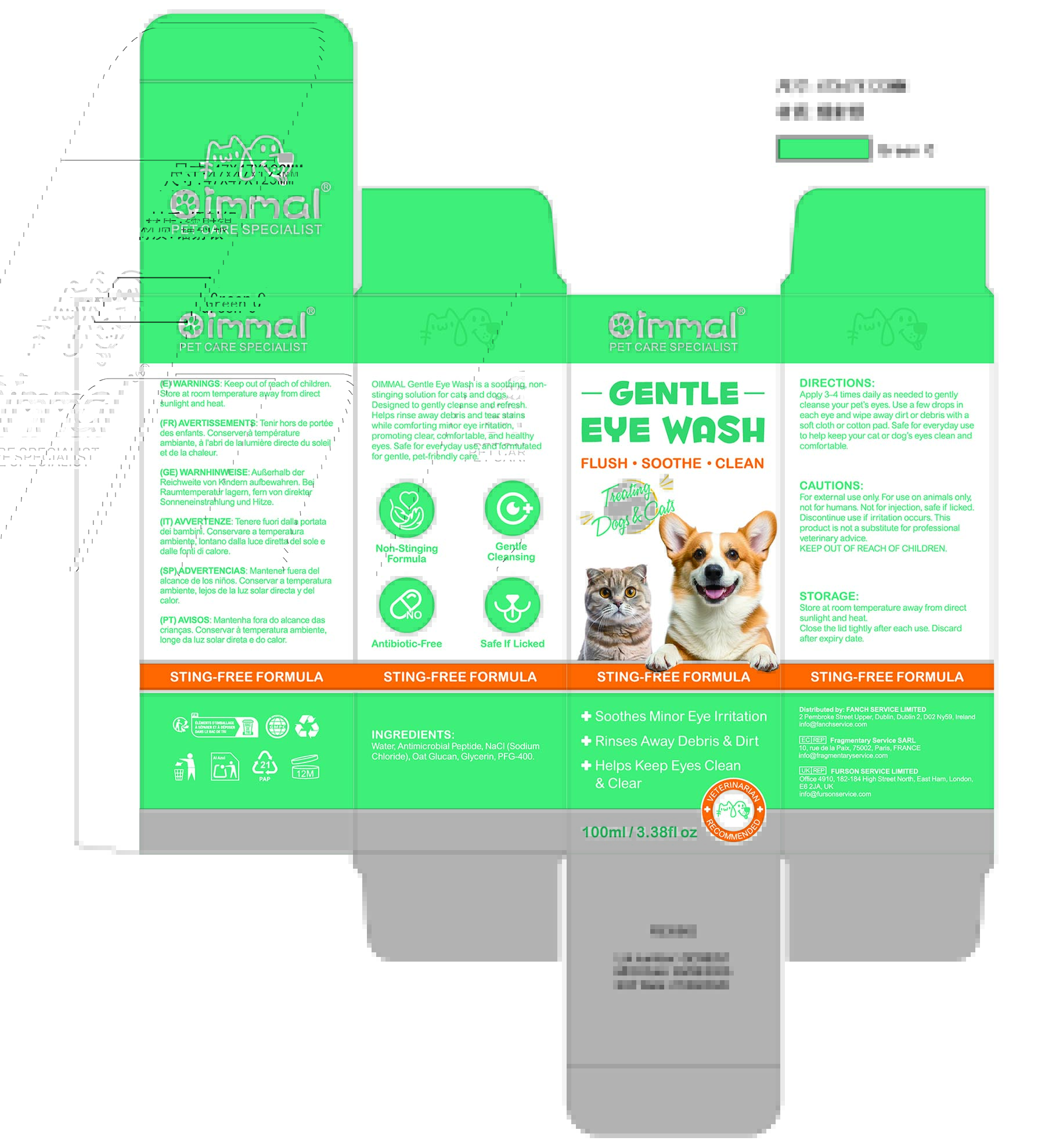 DRUG LABEL: Oimmal Gentle Eye Wash
NDC: 83804-016 | Form: LIQUID
Manufacturer: Shenzhen Shandian Jingling Technology Co., Ltd.
Category: otc | Type: HUMAN OTC DRUG LABEL
Date: 20260226

ACTIVE INGREDIENTS: SODIUM CHLORIDE 0.159 g/1 mL
INACTIVE INGREDIENTS: PEG-400; WATER; YEAST .BETA.-D-GLUCAN; GLYCERIN

83804-016 Oimmal Gentle Eye Wash

ACTIVE INGREDIENT

Sodium Chloride 15.9%

PURPOSE

eye care

INDICATIONS AND USAGE

OIMMAL Gentle Eye Wash is a soothing. non-stinging solution for cats and dogs.Designed to gently cleanse and refresh.Helps rinse away debris and tear stainswhile comforting minor eye irritation,promoting clear, comfortable, and healthyeyes. Safe for everyday use, and formulatedfor gentle, pet-friendly care.

WARNINGS

For external use only
For use on animais only.
not for humans.

DO NOT USE

not for humans. Not for injection, safe if licked.

WHEN USING

product is not a substitute for professional veterinary advice.

Discontinue use if irritation occurs.

KEEP OUT OF REACH OF CHILDREN.

DOSAGE AND ADMINISTRATION

Apply 3-4 times daily as needed to gentlycleanse your pet's eyes. Use a few drops ineach eye and wipe away dirt or debris with asoft cloth or cotton pad. Safe for everyday useto help keep your cat or dog's eyes clean andcomforlable.

INACTIVE INGREDIENT

Oat Glucan
WATER
PEG-400
Glycerin